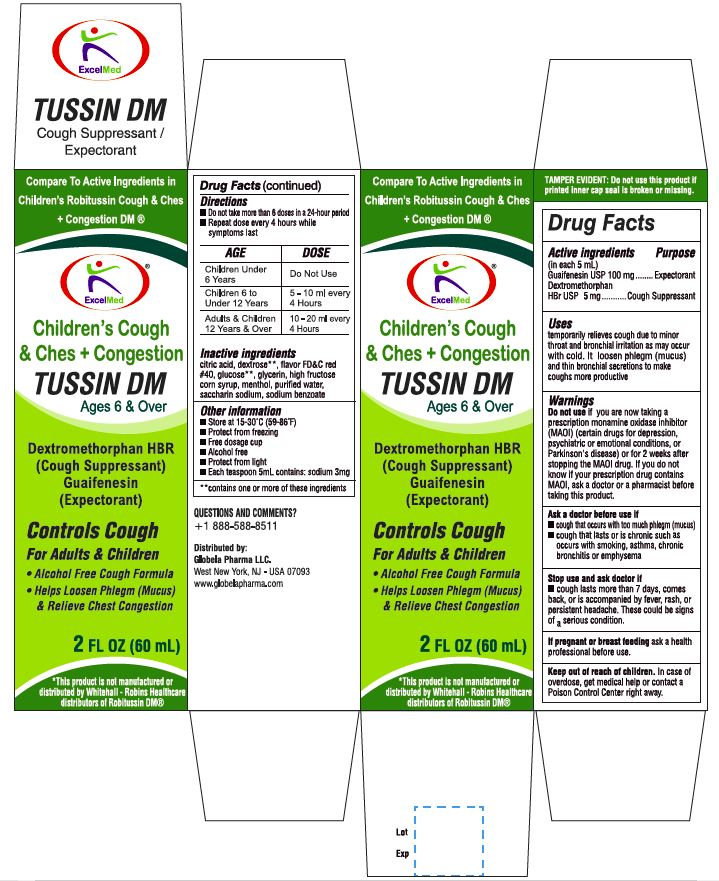 DRUG LABEL: Childrens Tussin DM
NDC: 71027-032 | Form: LIQUID
Manufacturer: KINGSTON PHARMA LLC
Category: otc | Type: HUMAN OTC DRUG LABEL
Date: 20170301

ACTIVE INGREDIENTS: DEXTROMETHORPHAN HYDROBROMIDE 5 mg/5 mL; GUAIFENESIN 100 mg/5 mL
INACTIVE INGREDIENTS: ANHYDROUS CITRIC ACID; FD&C BLUE NO. 1; FD&C RED NO. 40; SUCRALOSE; GLYCERIN; POLYETHYLENE GLYCOL, UNSPECIFIED; PROPYLENE GLYCOL; WATER; SODIUM CITRATE, UNSPECIFIED FORM; SODIUM BENZOATE

Children’s Tussin DM

Active Ingredient: Active Ingredient: Dextromethorphan HBr 5mg, Guaifenesin 100mg (in each 5 mL)

Purpose:
Cough suppressant
Expectorant

INDICATIONS AND USAGE

- temporarily relieves cough due to minor throat and bronchial irritation as may occur with a cold
- helps loosen phlegm (mucus) and thin bronchial secretions to coughs more productive

DO NOT USE IF PRINTED SEAL OVER IS TORN OR MISSING

Warnings:

Do not use if a child who is taking a prescription monoamine oxidase inhibitor (MAOI) (certain drugs for depression, psychiatric, or emotional conditions or parkinson’s disease), or for 2 weeks after stopping the MAOI drug. If you do not know if your child’s prescription drug contains an MAOI, ask a doctor or pharmacist before giving this product.

Ask a doctor before use if the child has

- Cough that occurs with too much phlegm (mucus)
- Persistent or chronic cough such as occurs with asthma

Stop use and ask doctor if cough lasts more than 7 days, comes back, or occurs with fever, rash, or persistent headache. These could be signs of a serious illness.

KEEP OUT OF REACH OF CHILDREN

Keep this and all drugs out of the reach of children. In case of overdose, seek professional assistance or contact a Poison control center right away.

Directions:

- This product does not contain directions or complete warnings for adult use.
- Use only enclosed dosing cup provided.
- Do not take more than 6 doses in any 24-hour period.
- Children 6 years to under 12 years: 5 mL – 10 mL taken every 4 hours.
- Children 4 years to under 6 years: 2.5 mL – 5 mL taken every 4 hours.
- Children under 4 years: do not use.

Other information

- each teaspoon contains: sodium 4 mg
- store at 20°-25°C (68°-77°F)

Inactive ingredients
Anhydrous citric acid, Artificial & Natural flavors, FD&C Blue#1, FD&C red 40, Sucralose, Glycerin, Polyethylen Glycol, Propylene Glycol, Purified Water, Sodium Citrate, Sodium Benzoate

HOW SUPPLIED

(packs: 4oz) Kingston NDC# 71027-036-04

Manufactured by: Kingston Pharma LLC
5 County Route 42
Massena, NY 13662